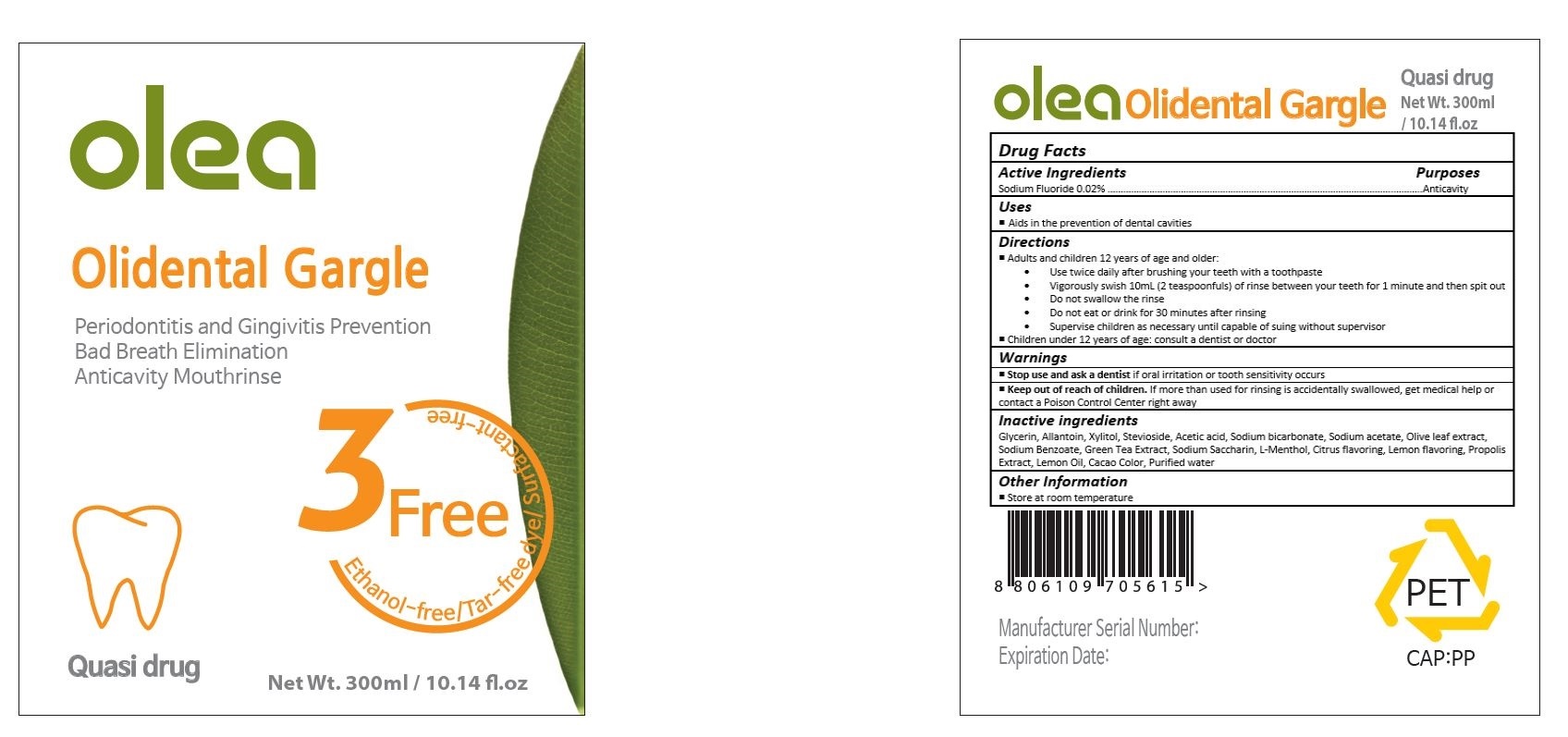 DRUG LABEL: Olidental Gargle
NDC: 70417-001 | Form: LIQUID
Manufacturer: AJU PHARM CO., LTD.
Category: otc | Type: HUMAN OTC DRUG LABEL
Date: 20160120

ACTIVE INGREDIENTS: SODIUM FLUORIDE 0.06 mg/300 mL
INACTIVE INGREDIENTS: GLYCERIN; ALLANTOIN; XYLITOL; STEVIOSIDE; ACETIC ACID; SODIUM BICARBONATE; SODIUM ACETATE; OLEA EUROPAEA LEAF; SODIUM BENZOATE; GREEN TEA LEAF; SACCHARIN SODIUM; LEVOMENTHOL; PROPOLIS WAX; LEMON OIL; WATER

Drug Facts

ACTIVE INGREDIENT

Sodium Fluoride 0.02%

PURPOSE

Anticavity

INDICATIONS AND USAGE

Aids in the prevention of dental cavities

DOSAGE AND ADMINISTRATION

Adults and children 12 years of age and older:
• Use twice daily after brushing your teeth with a toothpaste
• Vigorously swish 10mL (2 teaspoonfuls) of rinse between your teeth for 1 minute and then spit out
• Do not swallow the rinse
• Do not eat or drink for 30 minutes after rinsing
• Supervise children as necessary until capable of suing without supervisor

Children under 12 years of age: consult a dentist or doctor

Stop use and ask a dentist if oral irritation or tooth sensitivity occurs

Keep out of reach of children. If more than used for rinsing is accidentally swallowed, get medical help or contact a Poison Control Center right away

INACTIVE INGREDIENT

Glycerin, Allantoin, Xylitol, Stevioside, Acetic acid, Sodium bicarbonate, Sodium acetate, Olive leaf extract, Sodium Benzoate, Green Tea Extract, Sodium Saccharin, L-Menthol, Citrus flavoring, Lemon flavoring, Propolis Extract, Lemon Oil, Cacao Color, Purified water